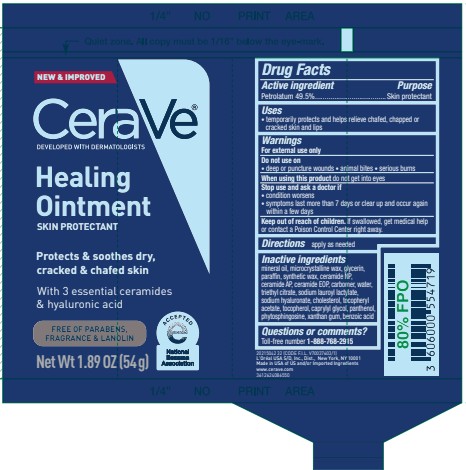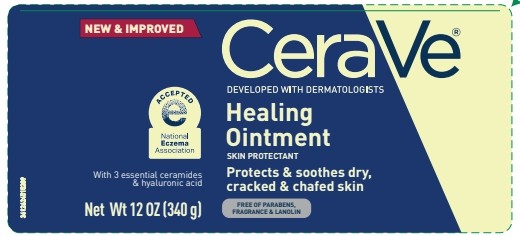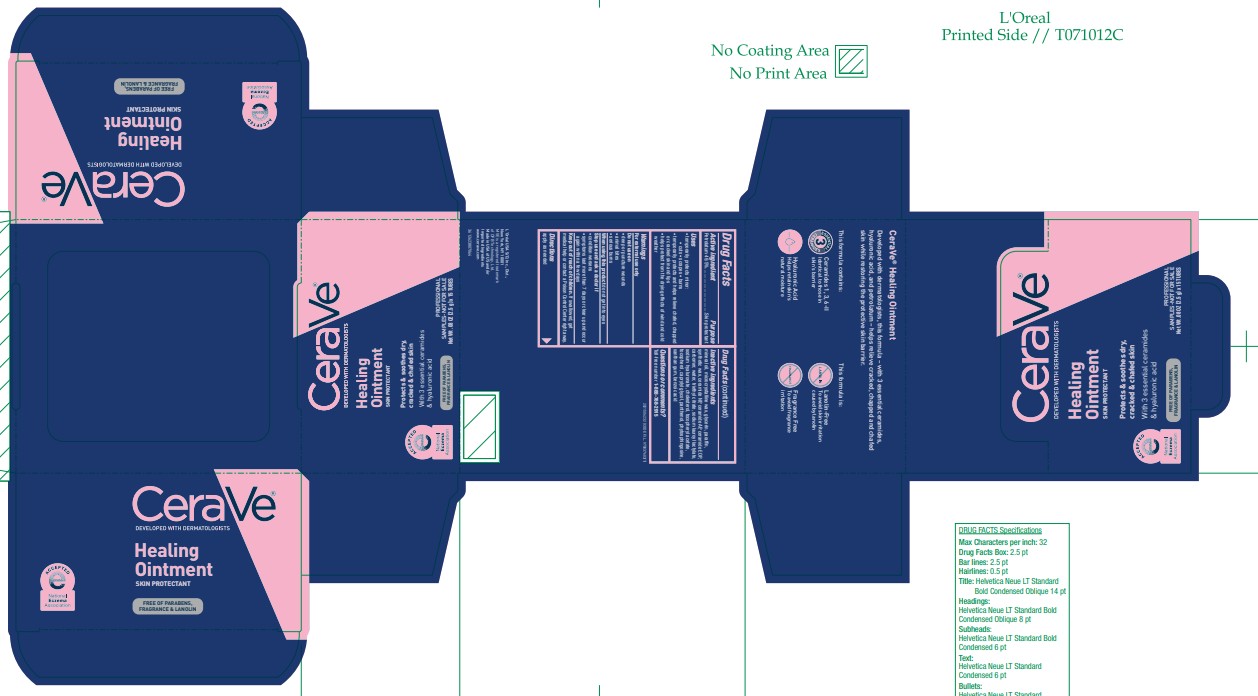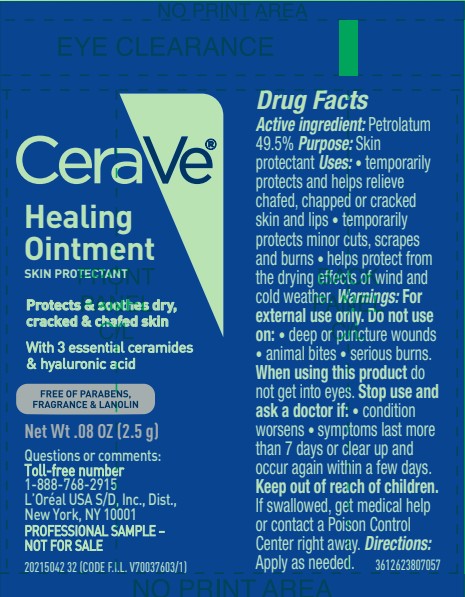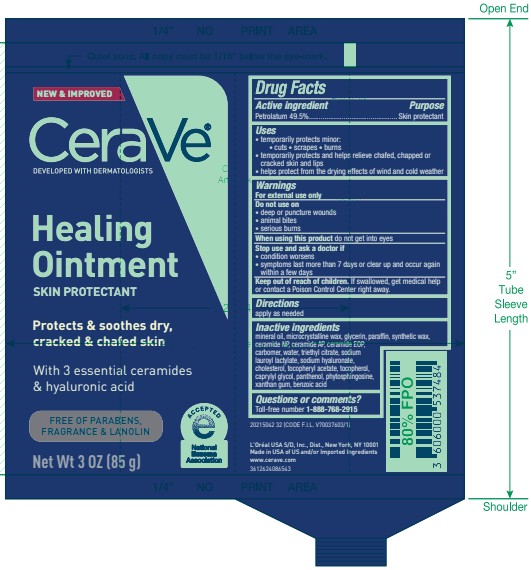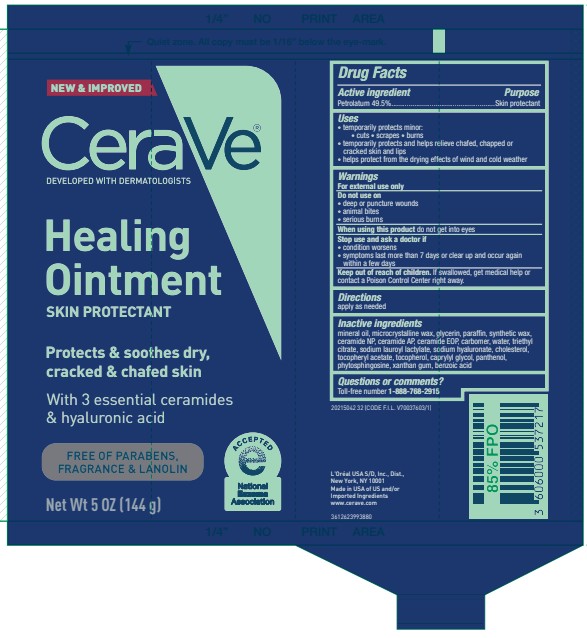 DRUG LABEL: Cerave Developed with Dermatologists Healing
NDC: 49967-721 | Form: OINTMENT
Manufacturer: L’Oreal USA Products Inc
Category: otc | Type: HUMAN OTC DRUG LABEL
Date: 20250701

ACTIVE INGREDIENTS: PETROLATUM 495 mg/1 g
INACTIVE INGREDIENTS: MINERAL OIL; MICROCRYSTALLINE WAX; GLYCERIN; PARAFFIN; CERAMIDE NP; CERAMIDE AP; CARBOMER; WATER; TRIETHYL CITRATE; SODIUM LAUROYL LACTYLATE; SODIUM HYALURONATE; CHOLESTEROL; .ALPHA.-TOCOPHEROL ACETATE; TOCOPHEROL; CAPRYLYL GLYCOL; PANTHENOL; PHYTOSPHINGOSINE; XANTHAN GUM; BENZOIC ACID; SYNTHETIC WAX (1200 MW)

Drug Facts

Active ingredient

Petrolatum 49.5%

Purpose

Skin protectant

Uses

temporarily protects minor:

• cuts • scrapes • burns

• temporarily protects and helps relieve chafed, chapped or cracked skin and lips

• helps protect from the drying effects of wind and cold weather

Warnings

For external use only

Do not use on

- deep or puncture wounds
- animal bites
- serious burns

When using this product

do not get into eyes

Stop use and ask a doctor if

- condition worsens
- symptoms last more than 7 days or clear up and occur again within a few days

Keep out of reach of children.

If swallowed, get medical help or contact a Poison Control Center right away.

Directions

apply as needed

Inactive ingredients

mineral oil, microcrystalline wax, glycerin, paraffin, synthetic wax,
ceramide NP, ceramide AP, ceramide EOP, carbomer, water, triethyl
citrate, sodium lauroyl lactylate, sodium hyaluronate, cholesterol,
tocopheryl acetate, tocopherol, caprylyl glycol, panthenol,
phytosphingosine, xanthan gum, benzoic acid

Questions or comments?

Toll-free number 1-888-768-2915